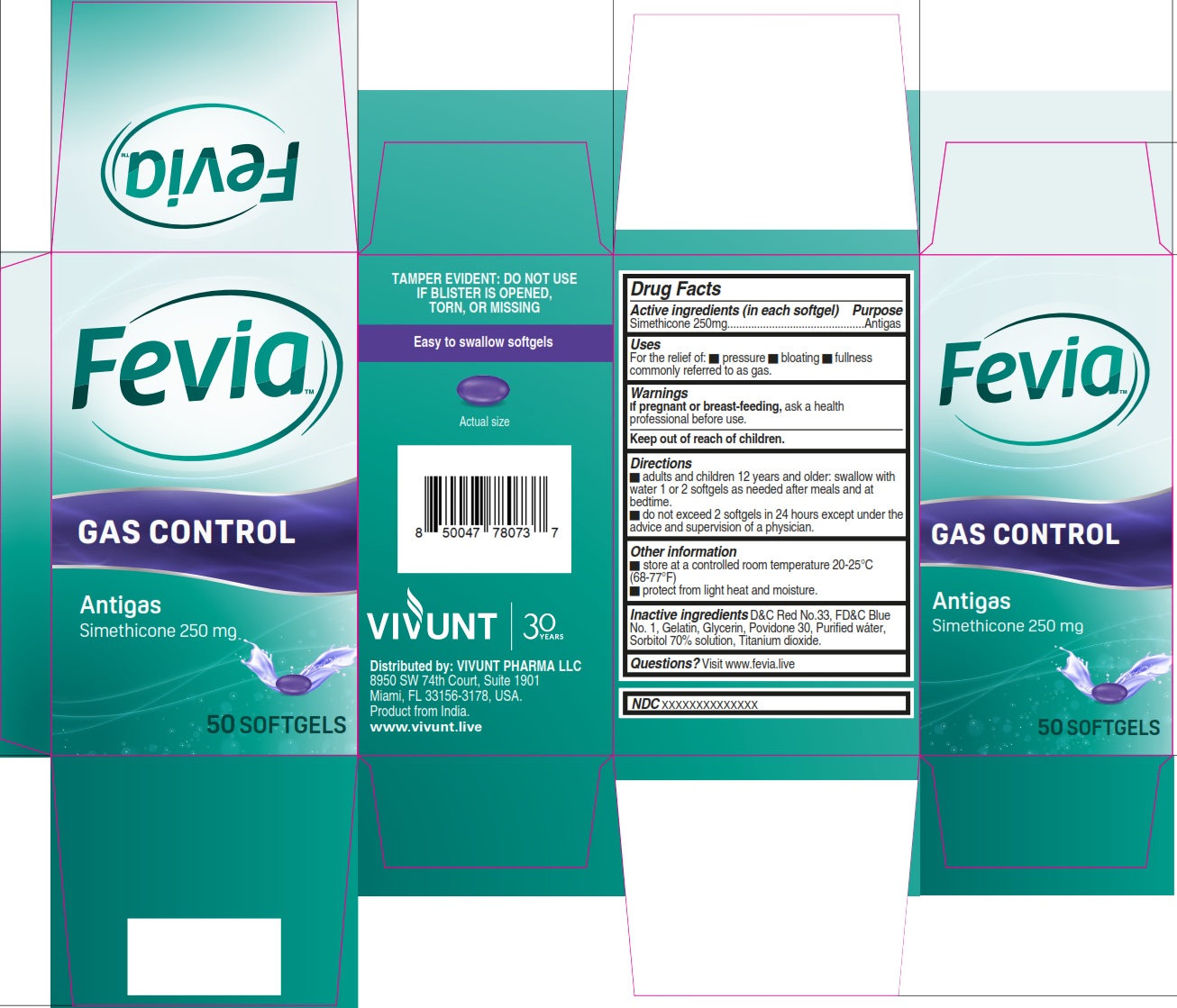 DRUG LABEL: FEVIA Gas Control
NDC: 82706-031 | Form: CAPSULE, LIQUID FILLED
Manufacturer: VIVUNT PHARMA LLC
Category: otc | Type: HUMAN OTC DRUG LABEL
Date: 20260226

ACTIVE INGREDIENTS: DIMETHICONE, UNSPECIFIED 250 mg/1 1
INACTIVE INGREDIENTS: FD&C BLUE NO. 1; GLYCERIN; GELATIN; TITANIUM DIOXIDE; SORBITOL SOLUTION 70%; POVIDONE K30; WATER; D&C RED NO. 33

FEVIA Gas Control 50

Drug Facts

Active ingredient (in each softgel)

- Simethicone 250 mg

Purpose

Antigas

Uses

for the relief of:

- Pressure, bloating, and fullness commonly referred to as gas.

Warnings

If pregnant or breast-feeding,

ask a health professional before use.

Keep out of reach of children.

Directions

- adults and children 12 years and older; swallow with water 1 or 2 softgels as needed after meals and at bedtime
- do not exceed 2 softgels in 24 hours except under the advice and supervision of a physician

Other information

- store at a controlled room temperature 20-25°C (68-77°F)
- protect from light and moisture

Inactive ingredients

D&C Red No.33, FD&C Blue No.1, Gelatin, Glycerin, Povidone 30, Purified water, Sorbitol 70% solution, Titanium dioxide.

Questions?

Visit www.fevia.live

Distributed by

VIVUNT

Distributed by: VIVUNT PHARMA LLC

8950 SW 74th Court, Suite 1901

Miami, FL 33156-3178, USA.

Product from India.www.vivunt.live

PACKAGE LABEL

Fevia™

GAS CONTROL

Antigas

Simethicone 250 mg

50 SOFTGELS

TAMPER EVIDENT: DO NOT USE IF BLISTER IS OPENED, TORN, OR MISSING

Easy to swallow softgels

Actual size